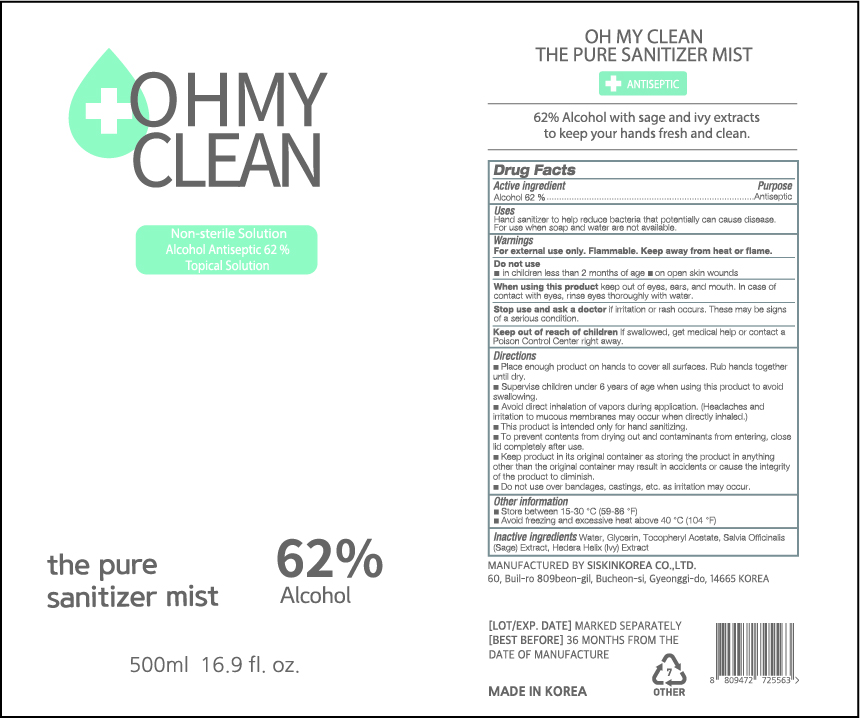 DRUG LABEL: OH MY CLEAN THE PURE SANITIZER MIST
NDC: 74514-9562 | Form: LIQUID
Manufacturer: SISKINKOREA CO.,LTD.
Category: otc | Type: HUMAN OTC DRUG LABEL
Date: 20200402

ACTIVE INGREDIENTS: ALCOHOL 310 mL/500 mL
INACTIVE INGREDIENTS: GLYCERIN; .ALPHA.-TOCOPHEROL ACETATE; SAGE; WATER; HEDERA HELIX LEAF

500ml_62%_mist_OH MY CLEAN THE PURE SANITIZER MIST [74514-9562-1]